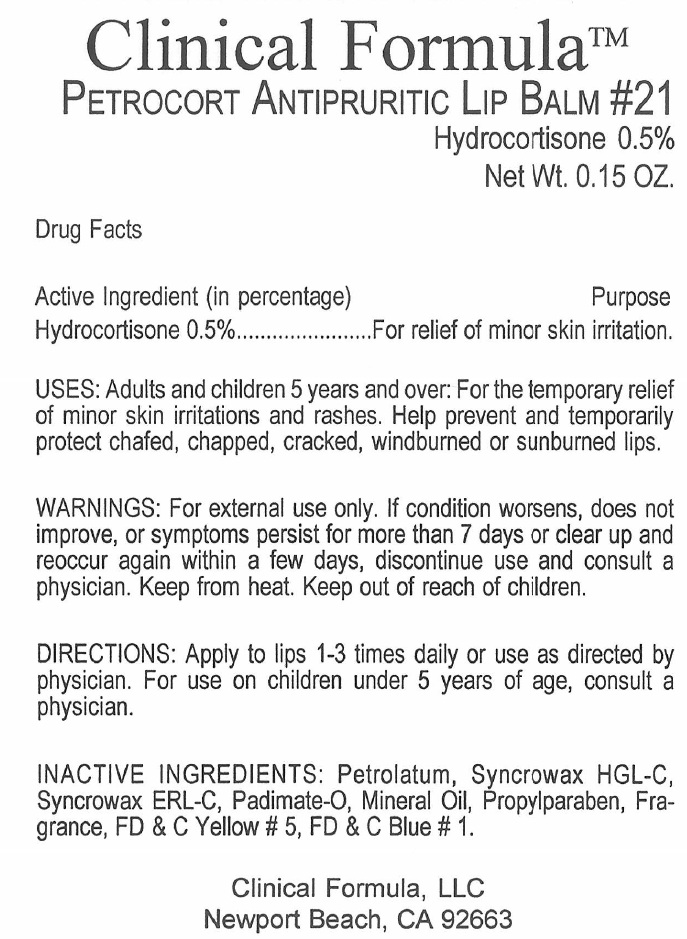 DRUG LABEL: Petrocort Antipruritic Lip 21
NDC: 51822-021 | Form: LIPSTICK
Manufacturer: Clinical Formula LLC
Category: otc | Type: HUMAN OTC DRUG LABEL
Date: 20231215

ACTIVE INGREDIENTS: HYDROCORTISONE 0.005 g/1 g
INACTIVE INGREDIENTS: PETROLATUM; C18-36 ACID TRIGLYCERIDE; PADIMATE O; MINERAL OIL; PROPYLPARABEN; FD&C YELLOW NO. 5; FD&C BLUE NO. 1

Petrocort Antipruritic Lip Balm #21

Active Ingredient (in percentage)

Hydrocortisone 0.5%

Purpose

For relief of minor skin irritation.

USES:

Adults and children 5 years and over: For the temporary relief of minor skin irritations and rashes. Help prevent and temporarily protect chafed, chapped, cracked, windburned or sunburned lips.

WARNINGS:

For external use only. If condition worsens, does not improve, or symptoms persist for more than 7 days or clear up and reoccur again within a few days, discontinue use and consult a physician. Keep from heat.

DIRECTIONS:

Apply to lips 1-3 times daily or use as directed by physician. For use on children under 5 years of age, consult a physician.

INACTIVE INGREDIENTS:

Petrolatum, Syncrowax HGL-C, Syncorwax ERL-C, Padimate-O Mineral Oil, Propylparaben, Fragrance, FD & C Yellow # 5, FD & C Blue # 1.